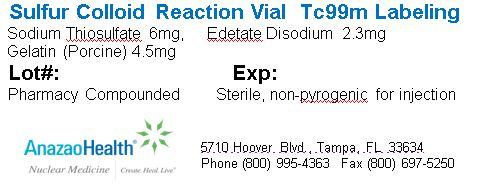 DRUG LABEL: Sulfur Colloid
NDC: 51808-220 | Form: INJECTION, POWDER, LYOPHILIZED, FOR SOLUTION
Manufacturer: AnazaoHealth Corporation
Category: prescription | Type: HUMAN PRESCRIPTION DRUG LABEL
Date: 20120701

ACTIVE INGREDIENTS: GELATIN 4.5 mg/1 1
INACTIVE INGREDIENTS: SODIUM THIOSULFATE 6 mg/1 1; EDETATE DISODIUM 2.3 mg/1 1

Sulfur Colloid Kit
(for the preparation of Tc99m-Sulfur Colloid injection)

DESCRIPTION

Dear Medical Professional,

AnazaoHealth Sulfur Colloid Kit consists of three separate nonradioactive components:

1. A 10 milliliter reaction vial containing: Sodium Thiosulfate, 4.8 mg, Gelatin (Porcine), 3.6 mg and Sodium Edetate, 2.3 mg. The contents of the vial are lyophilized and are under vacuum
2. Vial A, a 5 ml. vial containing:0.25 N. Hydrochloric Acid. The total volume in this vial is 1.2 mL.
3. Vial B, a 5 ml. vial containing:Sodium Hydroxide, 12 mg, Sodium Phosphate dibasic,15.7 mg, Sodium Phosphate, monobasic, 48.4 mg, Sterile Water for Injection. The total volume in this vial is 1.2 mL

INDICATIONS AND USAGE

Tc99m Sulfur Colloid is used in lymphoscintigraphy studies in breast cancer patients, for liver, spleen and bone marrow imaging and gastric transit studies and gastroesophageal reflux.

INSTRUCTIONS

Preparation of Technetium Tc 99m-Sulfur Colloid:

1. Collect components: 10 ml. Reaction Vial, Solution A, Solution B, Lead Pig, Boiling Water Bath.
2. Draw up 1 ml. Solution A. (HCl solution) in syringe.
3. Draw up 2.5 ml. Tc-99m Pertechnetate containing desired activity, dilute with sterile normal saline if necessary.
4. Add the 2.5 ml Tc-99m Pertechnetate to the shielded reaction vial.
5. Immediately add the 1 ml. Solution A.
6. Vent vial to release excess vacuum. Remove vent before boiling.
7. Shake gently to mix.
8. Place shielded vial in boiling water bath for 5 minutes for liver imaging and 3 minutes for lymphoscintigraphy imaging use.
9. Remove from boiling water and let cool for a few minutes.
10. Draw up 1 ml. Solution B. (Phosphate Buffer) while reaction vial is cooling
11. After cooling Reaction vial, add the 1 ml Solution B and shake gently to mix. Caution: be sure vial is cool to avoid excess pressure
12. Quality control: ITLC-SG in normal saline. Greater than 95% should stay at the origin
13. Tc 99m Sulfur Colloid expires 6 hours after mixing